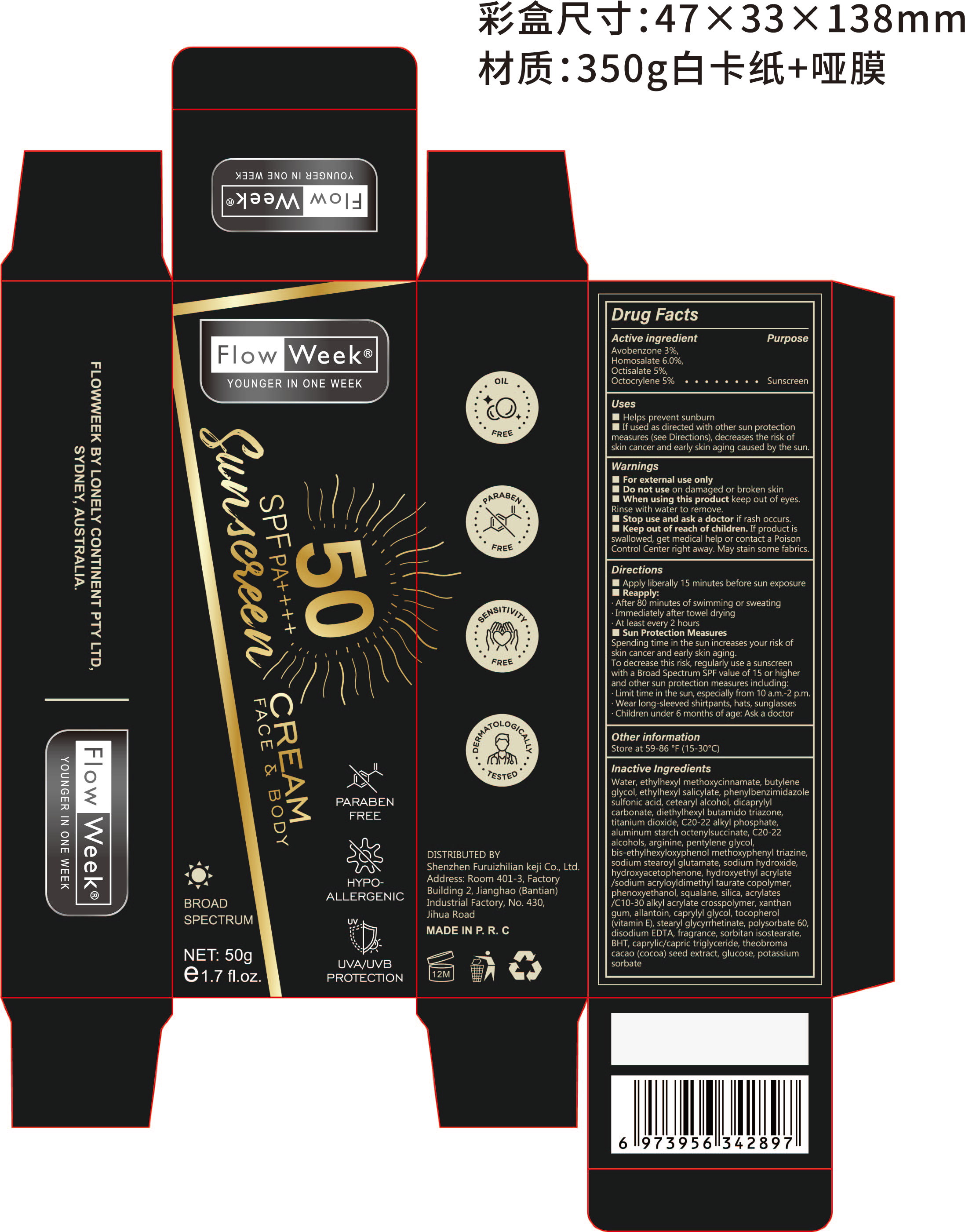 DRUG LABEL: Sunscreen Cream
NDC: 84445-005 | Form: LOTION, AUGMENTED
Manufacturer: Shenzhen Furuizhilian keji Co., Ltd.
Category: otc | Type: HUMAN OTC DRUG LABEL
Date: 20240716

ACTIVE INGREDIENTS: AVOBENZONE 1.5 g/50 g; HOMOSALATE 3 g/50 g; OCTISALATE 2.5 g/50 g; OCTOCRYLENE 2.5 g/50 g
INACTIVE INGREDIENTS: C20-22 ALCOHOLS; SODIUM HYDROXIDE; ACRYLATES/C10-30 ALKYL ACRYLATE CROSSPOLYMER (60000 MPA.S AT 1.0%); MEDIUM-CHAIN TRIGLYCERIDES; BEMOTRIZINOL; ARGININE; PENTYLENE GLYCOL; HYDROXYACETOPHENONE; COCOA; BUTYLENE GLYCOL; ISCOTRIZINOL; ALUMINUM STARCH OCTENYLSUCCINATE; HYDROXYETHYL ACRYLATE/SODIUM ACRYLOYLDIMETHYL TAURATE COPOLYMER (45000 MPA.S AT 1%); CAPRYLYL GLYCOL; TOCOPHEROL; STEARYL GLYCYRRHETINATE; SORBITAN ISOSTEARATE; BUTYLATED HYDROXYTOLUENE; ANHYDROUS DEXTROSE; POTASSIUM SORBATE; OCTINOXATE; ENSULIZOLE; XANTHAN GUM; ALLANTOIN; FRAGRANCE 13576; POLYSORBATE 60; EDETATE DISODIUM; WATER; CETOSTEARYL ALCOHOL; DICAPRYLYL CARBONATE; TITANIUM DIOXIDE; C20-22 ALKYL PHOSPHATE; SODIUM STEAROYL GLUTAMATE; PHENOXYETHANOL; SQUALANE; SILICON DIOXIDE

Sunscreen Cream

ACTIVE INGREDIENT

Avobenzone 3%, Homosalate 6%,Octisalate 5%, Octocrylene 5%

PURPOSE

Sunscreen

INDICATIONS AND USAGE

Helps prevent sunburn
if used as directed with other sun protection measures (see Directions), decreases the risk of skin cancer and early skin aging caused by the sun.

WARNINGS

For external use only

STOP USE

rash occurs

DO NOT USE

on damaged or broken skin

WHEN USING

keep out of eyes. Rinse with water to remone

KEEP OUT OF REACH OF CHILDREN

If product is swallowed, get medical help or contact a Poison Control Center right away. May stain some fabrics.

INACTIVE INGREDIENT

Water, Ethylhexyl Methoxycinnamate, Butylene Glycol, Ethylhexyl Salicylate, Phenylbenzimidazole Sulfonic Acid, Cetearyl Alcohol, Dicaprylyl Carbonate, Diethylhexyl Butamido Triazone, Titanium Dioxide, C20-22 Alkyl Phosphate, Aluminum Starch Octenylsuccinate, C20-22 Alcohols, Arginine, Pentylene Glycol, Bis-Ethylhexyloxyphenol Methoxyphenyl Triazine, Sodium Stearoyl Glutamate, Sodium Hydroxide, Hydroxyacetophenone, Hydroxyethyl Acrylate/Sodium Acryloyldimethyl Taurate Copolymer, Phenoxyethanol, Squalane, Silica, Acrylates/C10-30 Alkyl Acrylate Crosspolymer, Xanthan Gum, Allantoin, Caprylyl Glycol, Tocopherol (Vitamin E), Stearyl Glycyrrhetinate, Polysorbate 60, Disodium EDTA, Fragrance, Sorbitan Isostearate, BHT, Caprylic/Capric Triglyceride, Theobroma Cacao (Cocoa) Seed Extract, Glucose, Potassium Sorbate

DOSAGE AND ADMINISTRATION

Use when going out